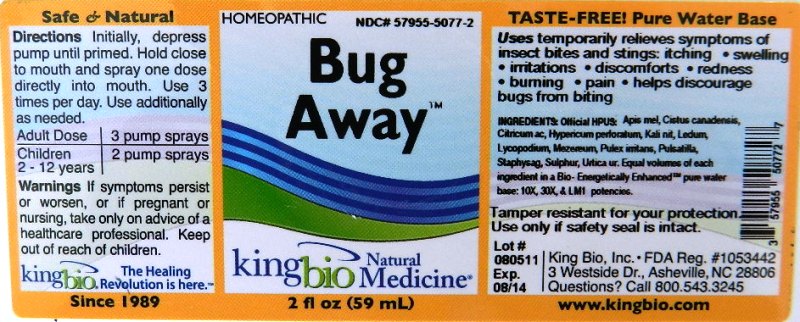 DRUG LABEL: Bug Away
NDC: 57955-5077 | Form: LIQUID
Manufacturer: King Bio Inc.
Category: homeopathic | Type: HUMAN OTC DRUG LABEL
Date: 20120118

ACTIVE INGREDIENTS: APIS MELLIFERA 10 [hp_X]/59 mL; HELIANTHEMUM CANADENSE 10 [hp_X]/59 mL; ANHYDROUS CITRIC ACID 10 [hp_X]/59 mL; HYPERICUM PERFORATUM 10 [hp_X]/59 mL; POTASSIUM NITRATE 10 [hp_X]/59 mL; LEDUM PALUSTRE TWIG 10 [hp_X]/59 mL; LYCOPODIUM CLAVATUM SPORE 10 [hp_X]/59 mL; DAPHNE MEZEREUM BARK 10 [hp_X]/59 mL; PULEX IRRITANS 10 [hp_X]/59 mL; PULSATILLA VULGARIS 10 [hp_X]/59 mL; DELPHINIUM STAPHISAGRIA SEED 10 [hp_X]/59 mL; SULFUR 10 [hp_X]/59 mL; URTICA URENS 10 [hp_X]/59 mL
INACTIVE INGREDIENTS: WATER

Bug Away

Active Ingredients

Official HPUS: Apis mellifica, Cistus canadensis, Citricum acidum, Hypericum perforatum, Kali nitricum, Ledum palustre, Lycopodium clavatum, Mezereum, Pulex irritans, Pulsatilla, Staphysagria, Sulphur and Urtica urens.

Reference image bug away.jpg

Inactive Ingredient

Equal volumes of each ingredient in a Bio-Energetically Enhanced pure water base. 10X, 30X and LM1 potencies.

Reference image bug away.jpg

Dosage and Administration

Directions: Initially, depress pump until primed. Hold close to mouth and spray one dose directly into mouth. Use 3 times daily. Use additionally as needed.

Adult Dose 3 pump sprays

Children 2-12 years 2 pump sprays

Reference image bug away.jpg

Purpose

Uses temporarily relieves symptoms of insect bites and stings:

- itching
- swelling
- irritations
- discomforts
- redness
- burning
- pain
- helps discourage bugs from biting

Reference image bug away.jpg

Warnings

If symptoms persist or worsen, or if pregnant or nursing, take only on advice of a healthcare professional.

Other Information: Tamper resistant for your protection. Use only if safety seal is intact.

Reference image bug away.jpg

Keep out of reach of children.

Reference image bug away.jpg

Indications and Usage

Uses temporarily relieves symptoms of insect bites and stings: itching, swelling, irritations, discomforts, redness, burning, pain and helps discourage bug from biting.

Reference image bug away.jpg

PACKAGE LABEL

King Bio Inc.

3 Westside Drive

Asheville, NC 28806

Questions? Call 800.543.3245

www.kingbio.com

Safe and Natural Homeopathic